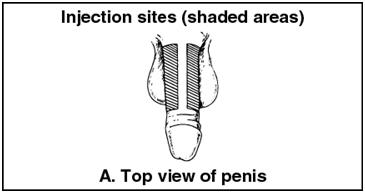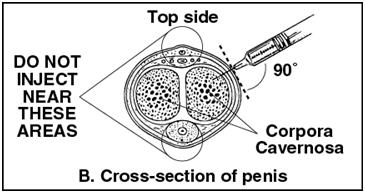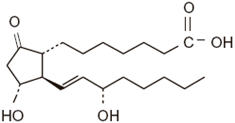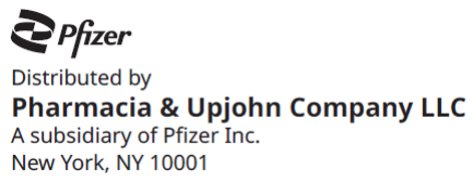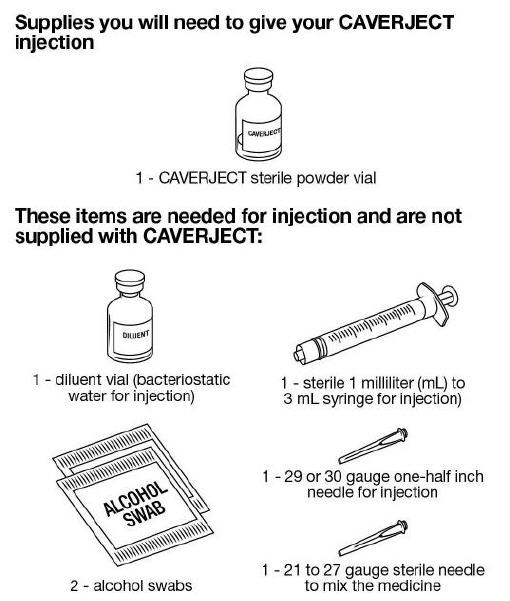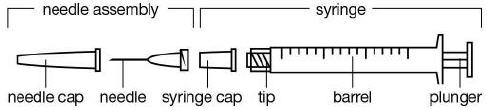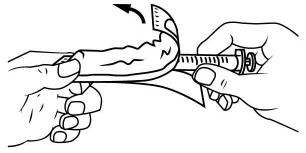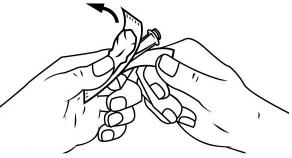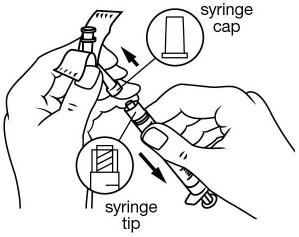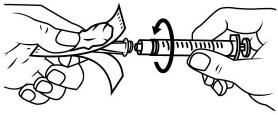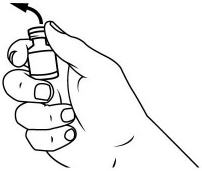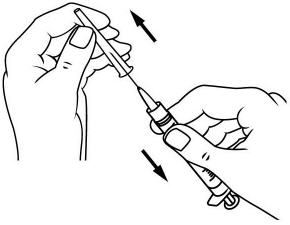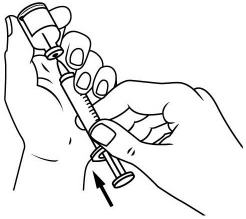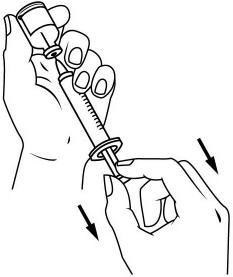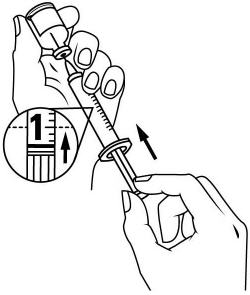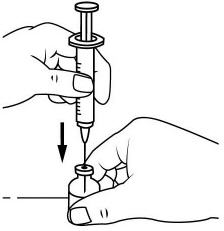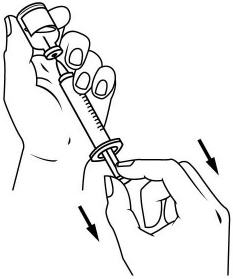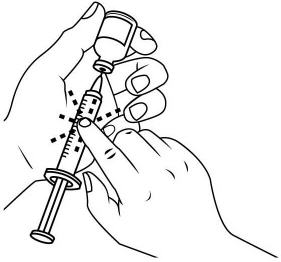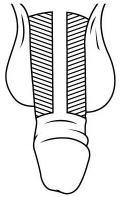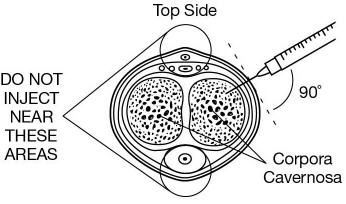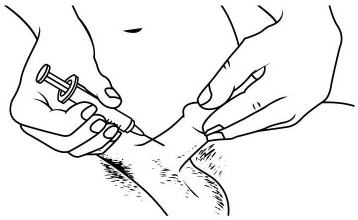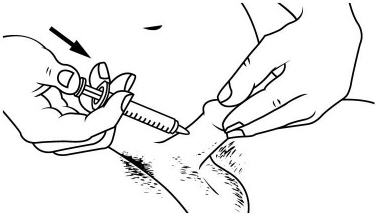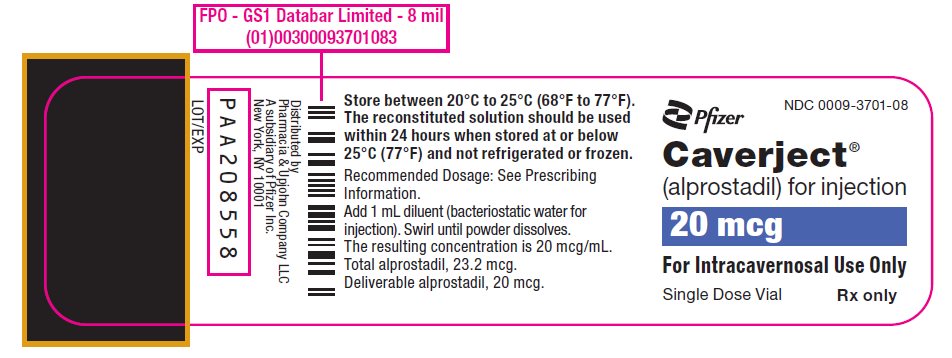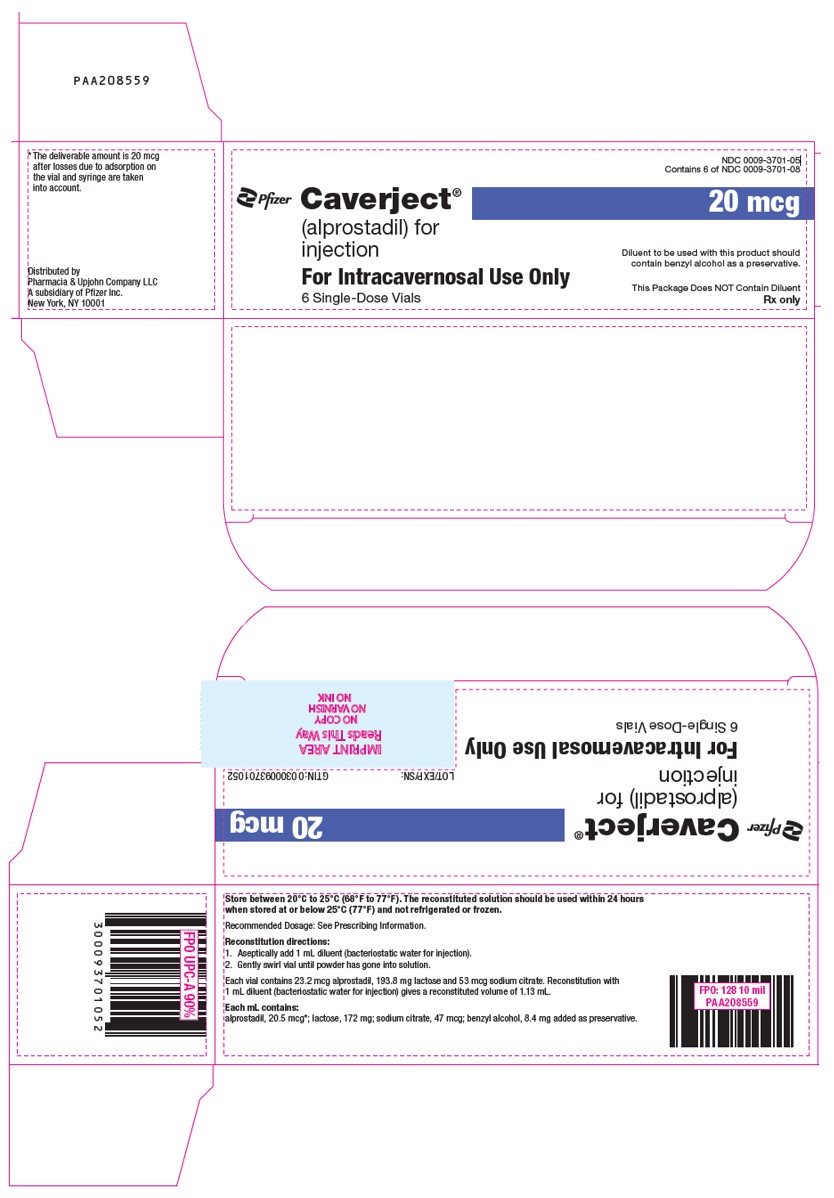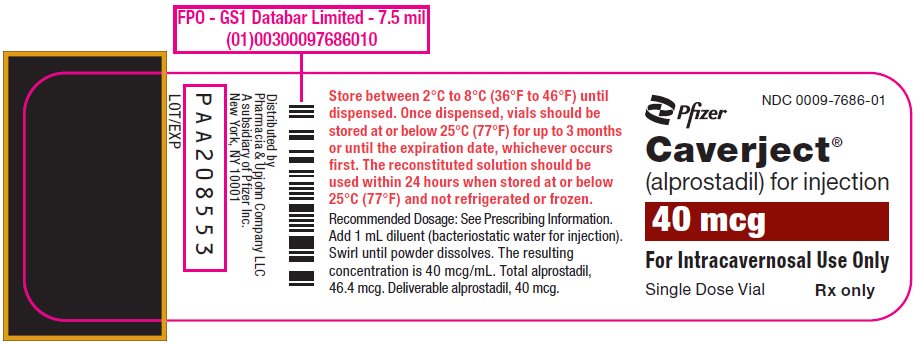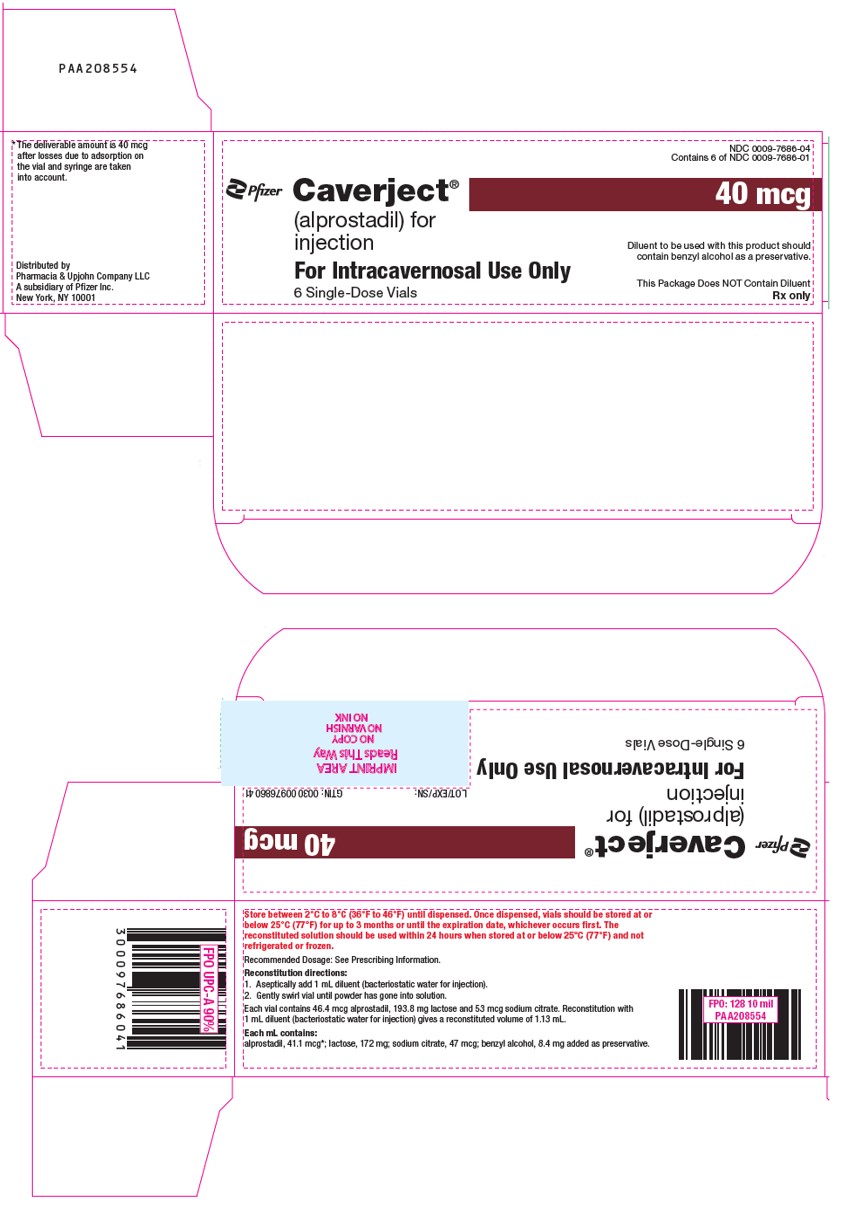 DRUG LABEL: Caverject
NDC: 0009-3701 | Form: INJECTION, POWDER, LYOPHILIZED, FOR SOLUTION
Manufacturer: Pharmacia & Upjohn Company LLC
Category: prescription | Type: HUMAN PRESCRIPTION DRUG LABEL
Date: 20240513

ACTIVE INGREDIENTS: ALPROSTADIL 20.5 ug/1 mL
INACTIVE INGREDIENTS: LACTOSE, UNSPECIFIED FORM 172 mg/1 mL; SODIUM CITRATE, UNSPECIFIED FORM 47 ug/1 mL; BENZYL ALCOHOL 8.4 mg/1 mL; HYDROCHLORIC ACID; SODIUM HYDROXIDE; WATER

HIGHLIGHTS OF PRESCRIBING INFORMATION

These highlights do not include all the information needed to use CAVERJECT safely and effectively. See full prescribing information for CAVERJECT.
CAVERJECT ® (alprostadil) for injection, for intracavernosal use
Initial U.S. Approval: 1981

1 INDICATIONS AND USAGE

CAVERJECT is a prostaglandin E1 agonist indicated

- For the treatment of erectile dysfunction (1.1).
- As an adjunct to other diagnostic tests in the diagnosis of erectile dysfunction (1.2).

2 DOSAGE AND ADMINISTRATION

- Determine the most suitable dose and presentation of CAVERJECT to use. Use a new vial for each dose of CAVERJECT (2.1).
- Administer first intracavernosal injections in the health care provider’s office and titrate the dose for each patient to the lowest effective dose (2.1).
- Instruct the patient on proper use and assess that they are well trained in the self-injection technique prior to initiation of at-home use (2.1).
- Recommended dosage for erectile dysfunction (2.2):
  - Erectile dysfunction of vasculogenic, psychogenic, or mixed etiology: Initiate dosing with 2.5 mcg
  - Erectile dysfunction of pure neurogenic etiology (spinal cord injury): Initiate dosing with 1.25 mcg
- Follow dose titration procedures for each type of erectile dysfunction and determine the maintenance dosage for patient home use in the health care provider’s office (2.2).
- The recommended frequency of injection is no more than 3 times weekly, with at least 24 hours between each dose (2.2).
- While on self-injection treatment, the patient should visit the prescribing health care provider’s office every 3 months to assess the efficacy and safety of the therapy (2.1).
- Follow the procedure for CAVERJECT syringe preparation (2.3).
- Follow procedure for CAVERJECT intracavernosal injection administration (2.4).
- To diagnose erectile dysfunction (pharmacologic testing), inject CAVERJECT intracavernosally and monitor patients for the occurrence of an erection (2.2).

3 DOSAGE FORMS AND STRENGTHS

For injection: 20 mcg/vial and 40 mcg/vial lyophilized powder in single-dose vials for reconstitution (3).

4 CONTRAINDICATIONS

- Men who have known hypersensitivity to the drug (4).
- Men who have conditions that predispose them to priapism, such as sickle cell anemia or sickle cell trait, multiple myeloma, or leukemia (4).
- Treatment of erectile dysfunction in men with fibrotic conditions of the penis, such as anatomical deformation, angulation, cavernosal fibrosis, or Peyronie's disease (4).
- Men with penile implants (4).

5 WARNINGS AND PRECAUTIONS

- Prolonged erection and priapism have occurred in patients receiving CAVERJECT. To minimize the chances of this occurring, titrate CAVERJECT slowly to the lowest effective dose (2.1). Advise patients to seek immediate medical assistance for an erection that persists longer than 4 hours (5.1).
- Penile fibrosis has occurred in patients receiving CAVERJECT. Follow patients regularly to detect signs of penile fibrosis. Discontinue in patients who develop penile angulation or cavernosal fibrosis (5.2).
- Hypotension: Injections of CAVERJECT can lead to increased peripheral blood levels of alprostadil, especially in patients with significant corpora cavernosa venous leakage. Avoid use in patients with known cavernosal venous leakage (5.3).
- Injection site bleeding may occur in patients taking anticoagulants, such as warfarin or heparin. Compress the site of injection with an alcohol swab or sterile gauze for 5 minutes (5.4).
- Cardiovascular risk related to underlying medical conditions: Underlying treatable medical causes of erectile dysfunction should be diagnosed and treated prior to initiation of therapy (5.5).
- Risks of use in combination with other vasoactive medications injected intracavernosally: Safety and efficacy of combinations of CAVERJECT and other vasoactive agents have not been systematically studied. Use of such combinations is not recommended (5.6).
- Needle breakage: A superfine needle is used for administration of CAVERJECT and cases of needle breakage have been reported. Careful instruction in proper patient handling and injection techniques may minimize this risk (5.7).
- Benzyl alcohol: Serious and fatal adverse reactions can occur in neonates and low birth weight infants treated with benzyl alcohol-preserved formulations in infusion solutions, including CAVERJECT. CAVERJECT is not indicated in neonates and infants (5.8).
- Counsel patients about sexually transmitted diseases: Counsel patients about the protective measures necessary to guard against sexually transmitted disease including the Human Immunodeficiency Virus (HIV) (5.9).

6 ADVERSE REACTIONS

The most common (≥10%) adverse reaction is penile pain (6.1).
To report SUSPECTED ADVERSE REACTIONS, contact Pfizer at (1-800-438-1985 and www.pfizer.com) or FDA at 1-800-FDA-1088 or www.fda.gov/medwatch.

FULL PRESCRIBING INFORMATION

1 INDICATIONS AND USAGE

1.1 Erectile Dysfunction

CAVERJECT is indicated for the treatment of erectile dysfunction.

1.2 Diagnostic Test

CAVERJECT is indicated as an adjunct to other diagnostic tests in the diagnosis of erectile dysfunction.

2 DOSAGE AND ADMINISTRATION

2.1 Important Dosage and Administration Instructions

- Alprostadil is available in different strengths and presentations. Determine the most suitable dose and presentation for each patient.
- CAVERJECT is available in single-dose vials containing 20 mcg or 40 mcg of alprostadil. Make sure a new, correct strength vial of CAVERJECT is used for each patient dosage preparation.
- Titrate the dose of CAVERJECT for each patient to the lowest effective dose.
- CAVERJECT doses greater than 60 mcg are not recommended.
- Administer the first injections of CAVERJECT in the health care provider’s office by medically trained personnel.
- Instruct the patient on proper use and assess that they are well trained in the self-injection technique prior to initiation of home use. Refer to the Patient Information and Instructions for Use.
- Re-evaluate patients regularly (every 3 months or as clinically appropriate) and determine if dosage adjustments are needed.

2.2 Recommended Dosage for Erectile Dysfunction

Erectile Dysfunction of Vasculogenic, Psychogenic, or Mixed Etiology

- Initiate dosing with 2.5 mcg of CAVERJECT intracavernosally, as recommended [see Dosage and Administration (2.4)].
- If there is a partial response at 2.5 mcg, administer another dose of 2.5 mcg within 1 hour. Use a new vial for each dose of CAVERJECT.
- During titration, no more than 2 doses should be given within a 24-hour period.
- If additional titration is required, administer doses in increments of 5 to 10 mcg at least 24 hours apart.
- The optimal dose should produce an erection suitable for intercourse that does not exceed a duration of 1 hour.
- The patient must stay in the health care provider’s office until complete detumescence occurs.

Repeat the titration as necessary until the optimal dose is achieved. Doses greater than 60 mcg are not recommended.

Erectile Dysfunction of Pure Neurogenic Etiology (e.g., Spinal Cord Injury).

- Initiate dosing with 1.25 mcg of CAVERJECT intracavernosally, as recommended [see Dosage and Administration (2.4)].
- If there is a partial response at 1.25 mcg, administer another dose of 1.25 mcg within 1 hour. Use a new vial for each dose of CAVERJECT.
- If additional titration is required, administer a dose of 5 mcg at least 24 hours later.
- During titration, no more than 2 doses should be given within a 24-hour period.
- The optimal dose should produce an erection suitable for intercourse that does not exceed a duration of 1 hour.
- The patient must stay in the health care provider’s office until complete detumescence occurs.

Repeat the titration as necessary until the optimal dose is achieved. Doses greater than 60 mcg are not recommended.

Maintenance Dosage for Patient Home Use

- Once the dose of CAVERJECT has been determined in the health care provider’s office, additional dose adjustment may be required after consultation with the health care provider. Adjust the dose in accordance with the titration guidelines described above.
- The recommended frequency of injection is no more than 3 times weekly, with at least 24 hours between each dose.

Adjunct to the Diagnosis of Erectile Dysfunction

As an adjunct to the diagnosis of erectile dysfunction, inject CAVERJECT intracavernosally and monitor patients for the occurrence of an erection. Extensions of this testing are the use of CAVERJECT as an adjunct to laboratory investigations, such as duplex or Doppler ultrasound imaging. For any of these tests, use a single dose of CAVERJECT that induces a rigid erection. Use the dose regimen for ‘Erectile Dysfunction of Vasculogenic, Psychogenic, or Mixed Etiology’ above.

2.3 Preparation Instructions

Supplies Needed and Not Supplied With CAVERJECT

- 1 mL of the diluent (bacteriostatic water for injection)
- 1 mL to 3 mL syringe, dependent on the titrated dose
- 21 to 27 gauge needle for reconstitution
- 29 or 30 gauge one-half inch needle for injection
- alcohol swabs

Reconstitution Instructions

- CAVERJECT vial(s): Using the correct strength vial containing 20 mcg or 40 mcg of CAVERJECT, use a 1 mL to 3 mL syringe, a 21 to 27 gauge needle, and 1 mL of the diluent (bacteriostatic water for injection) for reconstitution. Reconstitution results in CAVERJECT 20 mcg/mL or 40 mcg/mL.
- Visually inspect the solution in the vial for particulate matter and discoloration. Do not use the solution if it is cloudy, colored or contains particles.

Table 1: Volume of CAVERJECT Solution to Inject using 1 mL syringe
20 mcg Vial |  | 40 mcg Vial
Dose | Volume to Inject | Dose | Volume to Inject
1.25 mcg | 0.06 mL | 1.25 mcg | ---
2.5 mcg | 0.125 mL | 2.5 mcg | ---
5 mcg | 0.25 mL | 5 mcg | 0.125 mL
10 mcg | 0.5 mL | 10 mcg | 0.25 mL
15 mcg | 0.75 mL | 15 mcg | 0.375 mL
20 mcg | 1 mL | 20 mcg | 0.5 mL
25 mcg | --- | 25 mcg | 0.625 mL
30 mcg | --- | 30 mcg | 0.75 mL
40 mcg | --- | 40 mcg | 1 mL

- Draw the dose of CAVERJECT into the syringe.
- Replace the needle used for reconstitution with a 29 or 30 gauge one-half inch needle prior to injection.
- The reconstituted solution should be used within 24 hours when stored at or below 25°C (77°F).

Refer to the Patient Information and Instructions for Use in the FDA-approved patient labeling for the complete detailed instructions on reconstitution and needle preparation steps.

2.4 Administration Instructions

- Use a 29 or 30 gauge one-half inch needle for injecting each dose.
- The patient should be in a sitting or slightly reclined position when injecting a dose.
- Retract the foreskin in uncircumcised patients.
- Grasp the head of the penis with the thumb and forefinger and stretch it lengthwise along the thigh.
- The site of injection is either the right or left lateral penis. See Figures A and B below.

Figure A

Figure B

- Wipe the intended injection site with an alcohol swab prior to injection.
- Insert needle perpendicular to the long dorsolateral penile axis in the proximal third of penis. Avoid angulation of the syringe and do not bend the needle.
- Avoid visible veins during injection.
- With each use of CAVERJECT, alternate the side of the penis that is injected.
- Compress the site of injection with an alcohol swab or sterile gauze for 5 minutes.
- CAVERJECT is intended for single patient use only and should be discarded after use.

3 DOSAGE FORMS AND STRENGTHS

For injection: 20 mcg/vial and 40 mcg/vial lyophilized powder in single-dose vials for reconstitution.

4 CONTRAINDICATIONS

CAVERJECT is contraindicated:

- in men who have a known hypersensitivity to the drug [see Adverse Reactions (6.1)]
- in men who have conditions that predispose them to priapism, such as sickle cell anemia or sickle cell trait, multiple myeloma, or leukemia [see Warnings and Precautions (5.1)]
- for the treatment of erectile dysfunction in men with fibrotic conditions of the penis, such as anatomical deformation, angulation, cavernosal fibrosis, or Peyronie's disease [see Warnings and Precautions (5.2)]
- in men with penile implants.

5 WARNINGS AND PRECAUTIONS

5.1 Prolonged Erection and Priapism

Prolonged erection, defined as erection lasting between 4 to 6 hours in duration, occurred in 4% of 1,861 patients treated up to 18 months in studies of CAVERJECT. The incidence of priapism (erections lasting more than 6 hours in duration) was 0.4%. In the event of an erection that persists longer than 4 hours, the patient should seek immediate medical assistance. If priapism is not treated immediately, penile tissue damage and permanent loss of potency may result.

To minimize the chances of prolonged erection or priapism, titrate CAVERJECT to the lowest effective dose [see Dosage and Administration (2.1)]. In addition, do not use CAVERJECT in patients who have conditions that predispose them to priapism, such as sickle cell anemia or sickle cell trait, multiple myeloma, or leukemia [see Contraindications (4)].

5.2 Penile Fibrosis

The overall incidence of penile fibrosis reported in clinical studies with CAVERJECT was 3%. In one self-injection clinical study where duration of use was up to 18 months, the incidence of penile fibrosis was 7.8%.

Physical examination of the penis should be performed periodically, to detect signs of penile fibrosis. Treatment with CAVERJECT should be discontinued in patients who develop penile angulation or cavernosal fibrosis.

5.3 Hypotension

Intracavernous injections of CAVERJECT can increase peripheral blood levels of alprostadil which can result in hypotension. Avoid use of CAVERJECT in patients with known cavernosal venous leakage.

5.4 Injection Site Bleeding When Used with Anticoagulants

Patients on anticoagulants, such as warfarin or heparin, may have increased propensity for injection site bleeding after intracavernosal injection with CAVERJECT. Compress the site of injection with an alcohol swab or sterile gauze for 5 minutes.

5.5 Cardiovascular Risk Related to Underlying Medical Conditions

There is a potential for cardiac risk of sexual activity in patients with preexisting cardiovascular disease. Therefore, treatments for erectile dysfunction, including CAVERJECT, generally should not be used in men for whom sexual activity is inadvisable because of their underlying cardiovascular status. In addition, the evaluation of erectile dysfunction should include a determination of potential underlying causes and the identification of appropriate treatment following a complete medical assessment.

5.6 Risks of Use in Combination with Other Vasoactive Medications Injected Intracavernosally

The safety and efficacy of combinations of CAVERJECT and other vasoactive agents injected intracavernosally have not been established in clinical studies. The risks of prolonged erection, priapism, and hypotension may be increased.

5.7 Needle Breakage

Separate needles should be used for reconstitution and administration. A superfine needle is used for administration of CAVERJECT. As with all superfine needles, the possibility of needle breakage exists. Needle breakage, with a portion of the needle remaining in the penis, has been reported and, in some cases, has required hospitalization and surgical removal. Careful instruction in proper patient handling and injection techniques may minimize the potential for needle breakage [see Dosage and Administration (2.3) and Adverse Reactions (6.2)].

5.8 Risk of Serious Adverse Reactions in Infants due to Benzyl Alcohol Preservative

When reconstituted using the recommended diluent, the solution contains benzyl alcohol. Serious and fatal adverse reactions including "gasping syndrome" can occur in neonates and low birth weight infants treated with benzyl alcohol-preserved formulations in infusion solutions, including CAVERJECT. The "gasping syndrome" is characterized by central nervous system depression, metabolic acidosis, and gasping respirations. CAVERJECT is not indicated for use in pediatric patients.

5.9 Counsel Patients about Sexually Transmitted Diseases

The use of CAVERJECT offers no protection against sexually transmitted diseases. Counsel patients about the protective measures necessary to guard against sexually transmitted diseases, including the Human Immunodeficiency Virus (HIV).

6 ADVERSE REACTIONS

The following are described elsewhere in the labeling:

- Prolonged Erection and Priapism [see Warnings and Precautions (5.1)]
- Penile Fibrosis [see Warnings and Precautions (5.2)]

6.1 Clinical Trials Experience

Because clinical trials are conducted under widely varying conditions, adverse reaction rates observed in the clinical trials of a drug cannot be directly compared to rates in the clinical trials of another drug and may not reflect the rates observed in clinical practice.

Local Adverse Reactions: Local adverse reactions derived from 1861 patients in clinical studies of CAVERJECT, including an 18-month, open-label study, are shown in Table 2.

Table 2. Local Adverse Reactions Reported by ≥ 1% of Patients Treated with CAVERJECT for up to 18 Months
Penile pain | 37%
Prolonged erection | 4%
Penile fibrosis | 3%
Injection site hematoma | 3%
Penis disorder [Penis disorder includes: numbness, irritation, sensitivity, pruritus, erythema, skin tear, discoloration, itching.] | 3%
Injection site ecchymosis | 2%
Penile rash | 1%
Penile edema | 1%

The following local adverse reactions were reported in < 1% of patients: injection site hemorrhage, injection site inflammation, injection site itching, injection site swelling, injection site edema, urethral bleeding, penile warmth, numbness, irritation, sensitivity, pruritus, erythema, painful erection, and abnormal ejaculation.

In these studies, no local adverse reactions were reported in the 294 patients who received placebo, except for penile pain (2%).

Penile Pain: In the majority of the cases, penile pain was rated mild or moderate in intensity. Three percent of patients discontinued treatment because of penile pain

Prolonged Erection/Priapism: Prolonged erection was defined as an erection that lasted for 4 to 6 hours; priapism was defined as an erection that lasted 6 hours or longer. In clinical studies the frequency of prolonged erection after CAVERJECT was 4%, while the frequency of priapism was 0.4% [see Warnings and Precautions (5.1)].

Penile Hematoma/Ecchymosis: In clinical studies, the frequency of penile hematoma and ecchymosis was 3% and 2%, respectively.

Systemic Adverse Reactions: Systemic adverse reactions reported by ≥ 1% of subjects in clinical studies of CAVERJECT included: dizziness (1%).

The following systemic adverse reactions were reported in < 1% of patients: testicular pain, scrotal edema, hematuria, pelvic pain, hypotension, vasodilation, vasovagal reaction, diaphoresis, rash, and non-application site pruritus. Three patients (0.2%) discontinued due to symptomatic hypotension.

No systemic adverse reactions were reported in the 294 patients who received placebo.

In addition to the adverse reactions observed for CAVERJECT, the following adverse reactions have been reported in clinical studies of CAVERJECT IMPULSE:

CAVERJECT IMPULSE was evaluated in 87 patients in an open-label crossover study of 6 weeks treatment duration that compared the formulation of alprostadil for injection contained in CAVERJECT IMPULSE with the formulation contained in CAVERJECT. Doses used in this study ranged from 2.5 mcg to 20 mcg. Adverse reactions reported for the CAVERJECT IMPULSE formulation included: penis disorder (4.6%), prolonged erection (1.1%), injection site erythema (1.1%), rash (1.1%), dizziness (1.1%), and hematospermia (1.1%). Penis disorder included penile pain, post-injection pain, and pain with erection.

CAVERJECT IMPULSE was also evaluated in 63 patients in a single-dose, double-blind, crossover study that compared CAVERJECT IMPULSE with CAVERJECT. Doses used in this study ranged from 2.5 mcg to 20 mcg. Adverse reactions reported for the CAVERJECT IMPULSE formulation included: penile pain (1.6%) and pruritis (1.6%).

6.2 Postmarketing Experience

The following adverse reaction has been identified during post-approval use of CAVERJECT.

Because these reactions are reported voluntarily from a population of uncertain size, it is not always possible to reliably estimate their frequency or establish a causal relationship to drug exposure.

Injury and procedural complications: Needle breakage during administration of CAVERJECT. In some instances, surgical removal of the needle was required.

7 DRUG INTERACTIONS

The potential for pharmacokinetic drug-drug interactions between alprostadil and other agents administered orally or intracavernosally has not been formally studied [see Warnings and Precautions (5.6)].

8 USE IN SPECIFIC POPULATIONS

8.1 Pregnancy

CAVERJECT is not indicated for use in females.

8.2 Lactation

CAVERJECT is not indicated for use in females.

8.4 Pediatric Use

Safety and effectiveness have not been established in pediatric patients [see Warnings and Precautions (5.8)].

8.5 Geriatric Use

A total of 341 subjects included in clinical studies were 65 and older. No overall differences in safety and effectiveness were observed between these subjects and younger subjects, and the other reported clinical experience has not identified differences in responses between elderly and younger patients.

10 OVERDOSAGE

Overdosage was not observed in clinical trials with CAVERJECT. If intracavernous overdose of CAVERJECT occurs, the patient should be under medical supervision until any systemic effects have resolved and/or until penile detumescence has occurred. Treatment of any systemic symptoms (e.g., hypotension) would be appropriate.

11 DESCRIPTION

CAVERJECT contains alprostadil, a synthetic form of prostaglandin E1 (PGE1), and is designated chemically as (11α,13E,15S)-11,15-dihydroxy-9-oxoprost-13-en-1-oic acid. The molecular weight is 354.49.

Alprostadil is a white to off-white crystalline powder with a melting point between 115°C and 116° C. CAVERJECT is available as a sterile freeze-dried powder for intracavernosal use in sizes: 20 mcg and 40 mcg per vial. When reconstituted as directed with 1 mL of bacteriostatic water for injection, the volume of the reconstituted solution is 1.13 mL. Each mL of CAVERJECT contains 20.5 mcg or 41.1 mcg of alprostadil depending on vial strength, 172 mg of lactose, 47 mcg of sodium citrate and 8.4 mg of benzyl alcohol. The deliverable amount of alprostadil is 20 mcg or 40 mcg per mL because approximately 0.5 mcg for the 20 mcg strength and 1.1 mcg for the 40 mcg strength is lost due to adsorption to the vial and syringe. During manufacture, the pH of alprostadil for injection was adjusted with hydrochloric acid and/or sodium hydroxide before lyophilization.

The structural formula of alprostadil is represented below:

12 CLINICAL PHARMACOLOGY

12.1 Mechanism of Action

Alprostadil (PGE1) is a prostaglandin with a wide variety of pharmacological actions including vasodilation and inhibition of platelet aggregation. Alprostadil induces erection by relaxation of trabecular smooth muscle and by dilation of cavernosal arteries by binding to its receptors and increasing intracellular cyclic adenosine monophosphate (cAMP) levels via modulation of adenylate cyclase. This leads to expansion of lacunar spaces and entrapment of blood by compressing the venules against the tunica albuginea, a process referred to as the corporal veno-occlusive mechanism. Alprostadil also attenuates presynaptic noradrenaline release in the corpus cavernosum.

Studies in vitro have shown that alprostadil relaxed isolated preparations of human corpus cavernosum and spongiosum, as well as cavernous arterial segments contracted by either noradrenaline or PGF2α. In pigtail monkeys (Macaca nemestrina), alprostadil increased cavernous arterial blood flow in a dose-dependent manner in vivo.

12.3 Pharmacokinetics

Absorption: For the treatment of erectile dysfunction, alprostadil is administered by injection into the corpora cavernosa. The absolute bioavailability of alprostadil has not been determined.

Distribution: Following intracavernosal injection of 20 mcg alprostadil, mean peripheral plasma concentrations of alprostadil at 30 and 60 minutes after injection (89 picograms/mL and 102 picograms/mL, respectively) were not significantly greater than baseline levels of endogenous alprostadil (96 picograms/mL). Plasma levels of alprostadil were measured using a radioimmunoassay method. Alprostadil is bound in plasma primarily to albumin (81% bound) and to a lesser extent α-globulin IV-4 fraction (55% bound). No significant binding to erythrocytes or white blood cells was observed.

Metabolism: Alprostadil is converted to compounds which are further metabolized prior to excretion. Following intravenous administration, approximately 80% of circulating alprostadil is metabolized in one pass through the lungs, primarily by beta- and omega-oxidation. Following intracavernosal injection of 20 mcg alprostadil, peripheral levels of the major circulating metabolite, 13, 14-dihydro-15-oxo-PGE1, increased to reach a peak 30 minutes after injection and returned to pre-dose levels by 60 minutes after injection.

Excretion: The metabolites of alprostadil are excreted primarily by the kidney, with almost 90% of an administered intravenous dose excreted in urine within 24 hours post-dose. The remainder of the dose is excreted in the feces. There is no evidence of tissue retention of alprostadil or its metabolites following intravenous administration.

Pharmacokinetics in Specific Populations

Geriatric: The potential effect of age on the pharmacokinetics of alprostadil has not been formally evaluated.

Race: The potential effect of race on the pharmacokinetics of alprostadil has not been formally evaluated.

Renal and Hepatic Insufficiency: The pharmacokinetics of alprostadil have not been formally studied in patients with renal or hepatic insufficiency.

13 NONCLINICAL TOXICOLOGY

13.1 Carcinogenesis, Mutagenesis, Impairment of Fertility

Carcinogenesis

Long-term carcinogenicity studies have not been conducted.

Mutagenesis

Alprostadil was negative in bacterial mutation (Ames), alkaline elution, rat micronucleus, sister chromatid exchange, CHO/HGPRT mammalian cell forward gene mutation, and unscheduled DNA synthesis (UDS) assays.

Impairment of Fertility

Rat reproductive studies indicate that alprostadil at doses of up to 0.2 mg/kg/day does not adversely affect or alter male rat fertility. These doses are approximately 32-fold higher than the maximum recommended human dose of 60 mcg based on body surface area.

14 CLINICAL STUDIES

The efficacy of CAVERJECT was investigated in men with a diagnosis of erectile dysfunction due to psychogenic, vasculogenic, neurogenic, and/or mixed etiology in two double-blind, placebo-controlled studies (Study 1 and Study 2) and in one 6-month open-label study (Study 3). In clinical studies (Study 1 and Study 3), over 80% of patients experienced an erection sufficient for sexual intercourse after intracavernosal injection of CAVERJECT.

Study 1: A total of 153 men with ED with a mean age of 53 years (range 23–69 years) were enrolled. The study had three phases: a 2.5 week, randomized, double-blind, placebo-controlled crossover phase in which each man received in-office injections of placebo or 2.5 mcg, 5 mcg, 7.5 mcg, or 10 mcg of CAVERJECT; a 2 week, open-label, in-office dose-titration phase to identify the optimum home-use dose (the latter dose was defined as a dose inducing an erection sufficient for intercourse and lasting ≤ 60 minutes); and a 4-week open-label, at-home phase. In the double-blind placebo-controlled, crossover phase, each dose of CAVERJECT was significantly more effective than placebo by clinical evaluation ("full penile rigidity") and by RigiScan criteria (≥ 70% rigidity for at least 10 minutes); there was no response to placebo. The percentage of responders increased with increasing doses of CAVERJECT. The overall response rates in the crossover and dose-titration phases were 76% (117/153) by clinical evaluation and 51% (78/152) by RigiScan criteria. Seventy-three percent of the injections in 102 men who used CAVERJECT in the at-home phase resulted in satisfactory intercourse. Seventy-five percent of the men who used CAVERJECT in the at-home phase remained on the dose identified as optimum for them during the dose-titration phase; 17% and 8% of the men decreased or increased their dose, respectively. The mean duration of erection per injection was 70.8 minutes.

Study 2: A total of 296 men with ED with a mean age of 54 years (range 21–74 years) were enrolled in this double-blind, placebo-controlled, parallel-arm design study. The men were randomly assigned to one of five groups and received either a single dose of placebo, 2.5 mcg, 5 mcg, 10 mcg, or 20 mcg of CAVERJECT. No patient responded to placebo. The differences in the response rates in both the clinical and the RigiScan evaluations between each of the doses of CAVERJECT and placebo were statistically significant. There was also a statistically significant dose-response relationship with higher clinical response rates and higher RigiScan response rates with increasing doses of CAVERJECT (with exception of the 10-mcg dose). The mean duration of erection after injection ranged from 12 minutes after the 2.5-mcg dose to 44 minutes after the 20-mcg dose and the relationship was linear (p = .025, linear regression analysis).

Study 3: The efficacy of CAVERJECT was further evaluated in a 6-month, open-label, at-home study in 683 men with ED with a mean age of 58 years (range 20–79 years). The optimum dose of CAVERJECT was established by titration in 89% of men (606/683). A total of 471/683 men (69%) completed the 6-month study. Eighty-seven percent of the 13,762 injections of CAVERJECT administered resulted in satisfactory sexual activity. The mean duration of erection was 67.5 minutes.

The formulation of alprostadil contained in CAVERJECT IMPULSE was compared to CAVERJECT in 87 men with ED in a single-blind, crossover study. The doses used by the patients in the study ranged from 2.5 mcg to 20 mcg and were the same for both formulations. The efficacy of the two formulations was shown to be comparable, as assessed by the 30-point erectile function (EF) domain score from the International Index of Erectile Function (IIEF) and by a physician-assessment score for erectile response. The mean EF domain scores for CAVERJECT and the formulation contained in CAVERJECT were 26.6 (SD=5.3) and 27.6 (SD=3.8), respectively. The mean physician's assessment scores for CAVERJECT and the formulation contained in CAVERJECT IMPULSE were 2.6 (SD=0.6) and 2.7 (SD=0.5), respectively, based on a scale of 0 (no tumescence) to 3 (full rigidity).

16 HOW SUPPLIED/STORAGE AND HANDLING

CAVERJECT is a lyophilized powder supplied in vials containing 23.2 or 46.4 mcg of alprostadil for intracavernosal administration. When reconstituted as directed with 1 milliliter of bacteriostatic water for injection, the delivered amount of alprostadil is 20 mcg or 40 mcg.

STORAGE AND HANDLING

Store CAVERJECT 20 mcg vials between 20°C to 25°C (68°F to 77°F). The reconstituted solution should be used within 24 hours when stored at or below 25°C (77°F) and not refrigerated or frozen.

Store CAVERJECT 40 mcg vials between 2°C to 8°C (36° to 46°F) until dispensed. Once dispensed, vials should be stored at or below 25°C (77°F) for up to 3 months or until the expiration date, whichever occurs first. The reconstituted solution should be used within 24 hours when stored at or below 25°C (77°F) and not refrigerated or frozen.

When reconstituted and used as directed, the deliverable amount of alprostadil is 20 micrograms or 40 micrograms, respectively. Only bacteriostatic water for injection, should be used when reconstituting CAVERJECT.

CAVERJECT is available in the following packages:

Package of six 20 mcg vials | NDC 0009-3701-05
Package of six 40 mcg vials | NDC 0009-7686-04

The following supplies are needed for injection and are not supplied with CAVERJECT:

- 1 mL of the diluent (bacteriostatic water for injection)
- 1 mL to 3 mL syringe, dependent on the titrated dose
- 21 to 27 gauge needle for reconstitution
- 29 or 30 gauge one-half inch needle for injection
- alcohol swabs

17 PATIENT COUNSELING INFORMATION

Advise the patient to read the FDA-approved patient labeling (Patient Information and Instructions for Use).

Dosing and Self-Administration

To ensure safe and effective use of CAVERJECT, instruct and train the patient in the self-injection technique before he begins treatment with CAVERJECT, at home. Inform the patient the initial dose administration and dose titration will take place in the health care provider’s office [see Dosage and Administration (2.1)].

Once the home dose of CAVERJECT has been established, instruct the patient not to change the dose without consulting their health care provider.

The patient may expect an erection to occur within 5 minutes to 20 minutes and it should last no longer than 1 hour. CAVERJECT should be used no more than 3 times per week, with at least 24 hours between each use [see Dosage and Administration (2.2)].

Inform the patient that they must visit the health care provider’s office for regular check-ups for assessment of the therapeutic benefit and safety of treatment with CAVERJECT.

When self-administering the patient should be instructed to [see Dosage and Administration (2.2, 2.3)]:

- Discard any reconstituted solution with precipitates or discoloration
- Administer the injection along the dorso-lateral aspect of the proximal third of the penis
- Wipe the intended injection site with an alcohol swab prior to injection
- Avoid visible veins during injection
- Alternate the side of the penis that is injected and the site of injection
- Compress the site of injection with an alcohol swab or sterile gauze for 5 minutes
- Use each CAVERJECT vial only once and discard after use. Use a new vial of CAVERJECT for each dose.
- Not use a bent needle for reconstitution or injection. Do not attempt to straighten a bent needle. Remove the needle from the syringe, discard it, and attach a new, unused sterile needle to the syringe
- Not re-use or share needles and to properly discard after use.

Needle Breakage

Advise patients that needle breakage has occurred during self-injection of CAVERJECT. Advise patients to insert the needle perpendicular to the long axis of the penis to avoid bending or breakage of the needle [see Dosage and Administration (2.4), Warnings and Precautions (5.7) and Adverse Reactions (6.2)].

Penile Pain

Advise patients that the most frequently occurring side-effect is penile pain after injection and is usually mild to moderate in severity [see Adverse Reactions (6.1)].

Priapism

A potentially serious adverse reaction with CAVERJECT is priapism. Instruct the patient to seek immediate medical assistance if an erection persists for longer than 4 hours [see Warnings and Precautions (5.1)].

Penile Fibrosis

Penile fibrosis has been reported in clinical studies with CAVERJECT. Advise the patient to report any penile pain that was not present before or that increased in intensity, as well as the occurrence of nodules or hard tissue in the penis or curvature of the erect penis to his physician as soon as possible. [see Warnings and Precautions (5.2)].

Injection Site Reactions

Inform the patient that injection of CAVERJECT can induce a small amount of bleeding at the site of injection and that hematoma and ecchymosis may occur. Advise the patient to report any persistent redness, tenderness or swelling [see Warnings and Precautions (5.4)].

Sexually Transmitted Disease

Use of CAVERJECT offers no protection from the transmission of sexually transmitted diseases. Advise the patient about the protective measures that are necessary to guard against the spread of sexually transmitted diseases, including the human immunodeficiency virus (HIV) [see Warnings and Precautions (5.9)].

This product's labeling may have been updated. For the most recent prescribing information, please visit www.pfizer.com

LAB-0764-5.0

Patient Information

CAVERJECT [KAV-er-jeckt]®
(alprostadil)
for injection, for intracavernosal use

Read this Patient Information before you start using CAVERJECT and each time you get a refill. There may be new information. This information does not take the place of talking to your healthcare provider about your medical condition or your treatment.

What is CAVERJECT?

CAVERJECT is a prescription medicine used:

- to treat erectile dysfunction (ED).
- with other medical tests to diagnose ED.

CAVERJECT is not meant for use in women or children.

Do not use CAVERJECT if you:

- are allergic to alprostadil or any of the ingredients in CAVERJECT. See the end of this leaflet for a complete list of ingredients in CAVERJECT
- have certain medical problems that might cause you to have an erection that lasts for more than 4 hours, such as sickle cell anemia, sickle cell trait, multiple myeloma, leukemia
- have a deformed penis shape
- have a penile implant

Before you use CAVERJECT, tell your healthcare provider about all your other medical conditions, especially if you:

- have had an erection that lasted more than 4 hours
- have sickle cell trait or sickle cell anemia
- have or have had a blood cell cancer called multiple myeloma or leukemia
- have a deformed penis shape
- have a penile implant
- have low blood pressure (hypotension)
- have bleeding problems
- have or have had heart problems such as a heart attack, irregular heartbeat, angina, chest pain, narrowing of the aortic valve or heart failure

Tell your healthcare provider about all the medicines you take, including prescription and over-the-counter medicines, vitamins, and herbal supplements.

CAVERJECT may affect the way other medicines work, and other medicines may affect the way CAVERJECT works causing side effects.

Especially tell your healthcare provider if you take any other medicines that are treatments for ED, other medicines injected into your penis (intracavernosally), or certain medicines called anticoagulant medicines (such as heparin or warfarin).

Ask your healthcare provider or pharmacist for a list of these medicines if you are not sure.

Know the medicines you take. Keep a list of them to show to your healthcare provider and pharmacist when you get a new medicine.

How should I use CAVERJECT?

- See the detailed Instructions for Use that comes with your CAVERJECT for information about how to prepare and inject CAVERJECT the right way.
- You should receive your first dose of CAVERJECT in your healthcare provider's office.
- Use CAVERJECT exactly as your healthcare provider tells you to.
- Your healthcare provider will tell you how much CAVERJECT to use and when to use it.
- Your healthcare provider may change your dose if needed. Do not change your dose of CAVERJECT without first talking to your healthcare provider.
- Your healthcare provider should show you how to prepare and inject CAVERJECT the right way before you inject it for the first time.
- CAVERJECT should not be used more than 3 times per week.
- CAVERJECT should not be used more than 1 time every 24 hours.
- Change the exact place and side of the penis that you inject CAVERJECT each time you use it.
- CAVERJECT is for 1 time use only and should be thrown away properly after each use.

You should see your healthcare provider every 3 months for check-ups to be sure that CAVERJECT is working the right way and to change your CAVERJECT dose if needed.

What are the possible side effects of CAVERJECT?

CAVERJECT may cause serious side effects, including:

- an erection that will not go away (priapism). If you have an erection that lasts more than 4 hours, get medical help right away. If it is not treated right away, this condition can permanently damage your penis.
- deformed penis shape (penile fibrosis). Your healthcare provider should check your penis regularly for signs of penile fibrosis. You should not continue to use CAVERJECT if you get penile fibrosis.
- low blood pressure (hypotension).
- injection site bleeding. People who take certain medicines called anticoagulants (such as heparin or warfarin) may have a risk for increased bleeding at the injection site.
- increased risk of heart problems. Sexual activity can put an extra strain on your heart, especially if your heart is weak from a heart attack or heart disease. Ask your healthcare provider if your heart is healthy enough to handle the extra strain of having sex. Stop sexual activity and get medical help right away if you get symptoms of a heart problem such as chest pain, dizziness or nausea.
- needle breakage. There is a possibility of needle breakage with use of CAVERJECT. To best avoid breaking the needle, you should pay careful attention to your healthcare provider's instructions and handle the syringe and needle properly. If the needle is bent at any time, do not attempt to straighten it and do not use it. A bent and re-straightened needle is more likely to break. If the needle breaks during injection and you are able to see and grasp the broken end, you should remove it and contact your healthcare provider. If you cannot see or cannot grasp the broken end, you should promptly contact your healthcare provider.
- benzyl alcohol toxicity. Benzyl alcohol is a preservative that is present in CAVERJECT when it is mixed. Benzyl alcohol has caused serious side effects, including death, in children, especially premature and low-birth weight infants, who have received the preservative benzyl alcohol. CAVERJECT is not meant for use in children.

CAVERJECT does not protect you or your partner from getting sexually transmitted infections, including HIV-the virus that causes AIDS.

The most common side effect of CAVERJECT is penile pain

These are not all the possible side effects of CAVERJECT.

Call your doctor for medical advice about side effects. You may report side effects to FDA at 1-800-FDA-1088.

General information about the safe and effective use of CAVERJECT

Medicines are sometimes prescribed for purposes other than those listed in a Patient Information Leaflet. Do not use CAVERJECT for a condition for which it was not prescribed. Do not give CAVERJECT to other people even if they have the same symptoms that you have. It may harm them.

You can ask your pharmacist or healthcare provider for information about CAVERJECT that is written for health professionals.

What are the Ingredients in CAVERJECT?

Active ingredient: alprostadil

Inactive ingredients: lactose, sodium citrate, benzyl alcohol (contained in the final solution) and hydrochloric acid and/or sodium hydroxide for pH adjustment.

This product's labeling may have been updated. For the most recent prescribing information, please visit www.pfizer.com

LAB-1045-3.0

Revised: March 2023

INSTRUCTIONS FOR USE

CAVERJECT [KAV-er-jeckt]®
(alprostadil)
for injection, for intracavernosal use

Your healthcare provider should show you how to prepare and inject CAVERJECT the right way before you inject it for the first time. Do not try to inject yourself until you have been shown the right way to give your injections by your healthcare provider.

Information about how to safely inject CAVERJECT:

- Read and follow these instructions so that you inject CAVERJECT the right way. Call your healthcare provider if you have any questions about the right way to inject CAVERJECT.
- Separate needles should be used for reconstitution and administration. Do not use damaged or bent needles to inject CAVERJECT.
- If you accidentally bend a needle, do not attempt to straighten it.
- Using bent or re-straightened needles may cause part of the needle to break off and remain in the penis. Some people have reported needle breakage in their penis during the injection and, in some cases, had to go to hospital for surgery to remove the needle.
- If you accidentally bend the needle while preparing your CAVERJECT injection, remove it from the syringe, throw it away, and attach a new, needle to the syringe as described under "Prepare the Dose" below. (See "Dispose of your used CAVERJECT syringe and needle" at the end of these Instructions).
- Do not share your needles or syringes with other people, even if the needle has been changed. You may give other people a serious infection or get a serious infection from them.
- Use the needles, syringe, alcohol swabs, and vials only 1 time then safely throw away the supplies and any unused solution in a puncture resistant container (See "Dispose of your used CAVERJECT syringe and needle" at the end of these instructions). Ask your healthcare provider or pharmacist where you can get a puncture resistant or sharps container.

Supplies you will need to give your CAVERJECT injection (Figure A); - 1 CAVERJECT sterile powder vial; These items are needed for injection and are not supplied with CAVERJECT:; - 1 - diluent vial (bacteriostatic water for injection) - 1 - sterile 1 milliliter (mL) to 3 mL syringe - 1 - 21 to 27 gauge sterile needle to mix the medicine - 1 - 29 or 30 gauge one-half inch needle for injection - 2 - alcohol swabs - 1 - puncture-resistant or sharps container (not shown) for throwing away the used CAVERJECT syringe and needle. See "Dispose of your used CAVERJECT syringe and needle" at the end of these instructions. | Figure A: Supplies you will need for your Injection.
Follow the instructions below to prepare and give your injection. Figure B explains the parts of the needle and syringe that are referred to in the instructions. | Figure B: Parts of the needle and syringe

CAVERJECT comes in 20 mcg or 40 mcg strengths. Make sure you have the right strength vial of CAVERJECT that your healthcare provider prescribed for you.

Prepare the Syringe

Step 1.
Wash your hands thoroughly and dry them with a clean towel.
Step 2.
Assemble the needle and syringe as follows:; - Remove the syringe from its sterile wrapping. (Figure C) | Figure C: Remove the syringe
- Use a 21 to 27 gauge needle. Carefully pull the wrapper tabs back enough to expose the sterile open end of the needle assembly. Do not completely remove the wrapper. - Do not touch the open end of the needle (Figure D). | Figure D: Open the needle wrapper
Step 3.
Keeping hold of the needle assembly, remove the plastic syringe cap from the syringe tip (Figure E). Do not touch the syringe tip. | Figure E: Remove the syringe cap
Step 4.
Hold the needle assembly (still in the paper wrapper). Firmly attach the needle to the syringe tip. Turn it clockwise, like tightening a screw to lock it in place (Figure F).; - With the needle cover in place, set the syringe and needle down on a clean, level surface, like a table. | Figure F: Attach the needle to the syringe
Mixing the powder and liquid to prepare the dose
Step 5.
Remove the plastic cap from the vial of CAVERJECT and remove any cover from the diluent (Figure G). | Figure G: Remove the vial cap
Step 6.
Wipe the rubber stoppers on the vials of CAVERJECT and diluent with 1 alcohol swab. Throw away the alcohol swab.
Step 7.
Carefully hold the syringe by the barrel and remove the needle cover (Figure H).; - Do not discard the needle cover, you will need to use it again (see step 13). - Do not touch the needle. | Figure H: Remove the needle cover
Step 8.
Hold the syringe with the needle attached and push the needle through the center of the diluent vial's rubber stopper (Figure I). Be careful not to bend the needle. | Figure I: Push the needle into the diluent vial
- Keeping the needle in the vial, firmly hold the vial and syringe upside down in one hand (see Figure J). - Keep the needle tip below the level of the liquid and pull back on the syringe plunger until all the diluent is removed from vial. | Figure J: Remove the liquid from the vial
Step 9.
Push the syringe plunger to the 1mL mark on the syringe. This will remove air and extra liquid back into vial. Grasp the side of the syringe barrel (not the plunger) and pull the needle from the diluent vial in a straight line to avoid bending the needle (Figure K). | Figure K: Adjust the amount of liquid in the syringe
Step 10.
Holding the syringe with the needle attached in a straight line with the vial of CAVERJECT, push the needle through the center of the rubber stopper of the vial of CAVERJECT. Be careful not to bend the needle.; - Push the syringe plunger all the way down to move all the liquid into the vial. Go immediately to step 11. | Figure L: Push the needle into the CAVERJECT vial
Step 11.
Without removing the needle or touching the needle or stopper, gently swirl (do not shake) the vial until all the powder is dissolved in the liquid. Then turn the vial and needle/syringe upside down and gently swirl the vial to dissolve any powder in the neck of the vial. Do not use the solution if it is cloudy, colored, or contains particles.
Step 12.
Keeping the needle in the vial, firmly hold the vial and syringe upside down in one hand.; - Keeping the needle tip below the level of the liquid, slowly pull back on the syringe plunger until all the liquid is removed from the vial (see Figure M). | Figure M: Remove the liquid from the vial
Step 13.
If there are air bubbles, gently tap the syringe barrel until the bubbles float to the top of the liquid (see Figure N).; - Holding the syringe upright, push the syringe plunger to the correct volume mark for the dose prescribed by your healthcare provider. This will remove any air and extra liquid into the vial. - Grasp the syringe barrel (not the plunger) and pull the needle/syringe straight out of the vial of CAVERJECT in a straight line to avoid and be sure not to bend the needle. - Carefully replace the needle cover over the needle that you used to mix the liquid. | Figure N: Tap the syringe barrel to remove air bubbles
Step 14.
Carefully replace the needle used to mix the liquid with a new 29 to 30 gauge one half inch needle for your injection.
- Remove the old needle from the syringe and immediately throw it away in an FDA-cleared sharps disposal container.
- Unwrap the new needle as in step 2.
- Attach the new needle as in step 3.
Set the syringe down on a level surface.
How to give the injection
- Make yourself comfortable. You should be sitting upright or slightly reclined when injecting CAVERJECT.
- Make sure that the needle is not bent. If it is, do not use it. Do not attempt to straighten the needle out. Properly throw away any bent needles.
STEP 15.
The injection will go into the part of the penis shown as the shaded area in Figure O. Do not inject CAVERJECT into the white areas because there may be blood vessels in the white areas. (See Figure P).; - The correct injection angle and depth of injection is shown in Figure P. - With each injection of CAVERJECT change the side of the shaft of the penis, and choose a different location for each injection, as shown in the shaded area in Figure O. | Figure O: Top view of the penis showing injection sites (shaded areas).; Figure P: Cross-section of the penis
Step 16.
Wipe the area for injection with an alcohol swab and let it dry.
Step 17.
Do not throw away the swab; you will need to use it again after you give your injection. (See Step 23).
Step 18.
If your penis is not circumcised, pull the foreskin back. Take hold of the tip of your penis with your thumb and forefinger; stretch it lengthwise along your thigh.
Step 19.
Gently squeeze your penis between your thumb and finger so that the injection site bulges out.
Step 20.
Remove the cover from the needle. Position your penis firmly against your thigh to keep it from moving during the injection.
Step 21.
Keeping a firm grip on your penis, take the syringe in your other hand, and push the needle straight into the selected injection site (See Figure Q).; - Refer to Figure P for the correct angle and depth of injection. - Do not inject CAVERJECT into veins or other blood vessels (the white areas in Figure O). | Figure Q: Insert the needle into the injection site
Step 22.
Holding the syringe barrel between two fingers, move your thumb or finger to the top of the plunger and, with a steady motion, push down on the plunger so that the entire contents of the syringe is slowly injected (Figure R). | Figure R: Inject the contents of the syringe.
Step 23.
After completing the injection, carefully pull the needle out of your penis. Press gently on the injection site with the alcohol swab for about 5 minutes or until bleeding stops.

After your injection:

Dispose of your used CAVERJECT syringe and needles.

- Put your used CAVERJECT syringe and needles in a FDA-cleared sharps disposal container right away after use. Do not throw away loose needles and syringes in your household trash.
- If you do not have a FDA-cleared sharps disposal container, you may use a household container that is:
  - made of a heavy-duty plastic
  - can be closed with a tight-fitting, puncture-resistant lid, without sharps being able to come out
  - upright and stable during use
  - leak-resistant
  - properly labeled to warn of hazardous waste inside the container
- When your sharps disposal container is almost full, you will need to follow your community guidelines for the right way to dispose of your sharps disposal container. There may be state or local laws about how you should throw away used needles and syringes. Do not reuse or share your needles or syringes with other people. For more information about the safe sharps disposal, and for specific information about sharps disposal in the state that you live in, go to the FDA's website at: http://www.fda.gov/safesharpsdisposal.
- Do not dispose of your used sharps disposal container in your household trash unless your community guidelines permit this. Do not recycle your used sharps disposal container.

How should I store CAVERJECT?

CAVERJECT 20 mcg vial storage information

1. Store CAVERJECT 20 mcg vials between 20°C to 25°C (68°F to 77°F).
2. The reconstituted solution should be used within 24 hours when stored at or below 25°C (77°F) and not refrigerated or frozen.

CAVERJECT 40 mcg vial storage information

1. Store CAVERJECT 40 mcg vials between 2°C to 8°C (36°F to 46°F) until dispensed. Once dispensed, vials should be stored at or below 25°C (77°F) for up to 3 months or until the expiration date, whichever occurs first.
2. The reconstituted solution should be used within 24 hours when stored at or below 25°C (77°F) and not refrigerated or frozen.

Keep CAVERJECT and all medicines out of the reach of children.

This Patient Information and Instructions for Use has been approved by the U.S Food and Drug Administration.

LAB-0009-8.0

Revised March 2023

PRINCIPAL DISPLAY PANEL - 20 mcg Vial Label

NDC 0009-3701-08

Pfizer

Caverject®
(alprostadil) for injection

20 mcg

For Intracavernosal Use Only

Single Dose Vial
Rx only

PRINCIPAL DISPLAY PANEL - 20 mcg Vial Package

NDC 0009-3701-05
Contains 6 of NDC 0009-3701-08

Pfizer
Caverject®

(alprostadil) for
injection

For Intracavernosal Use Only

6 Single-Dose Vials

20 mcg

Diluent to be used with this product should
contain benzyl alcohol as a preservative.

This Package Does NOT Contain Diluent
Rx only

PRINCIPAL DISPLAY PANEL - 40 mcg Vial Label

NDC 0009-7686-01

Pfizer

Caverject®
(alprostadil) for injection

40 mcg

For Intracavernosal Use Only

Single Dose Vial
Rx only

PRINCIPAL DISPLAY PANEL - 40 mcg Vial Package

NDC 0009-7686-04
Contains 6 of NDC 0009-7686-01

Pfizer
Caverject®

(alprostadil) for
injection

For Intracavernosal Use Only

6 Single-Dose Vials

40 mcg

Diluent to be used with this product should
contain benzyl alcohol as a preservative.

This Package Does NOT Contain Diluent
Rx only